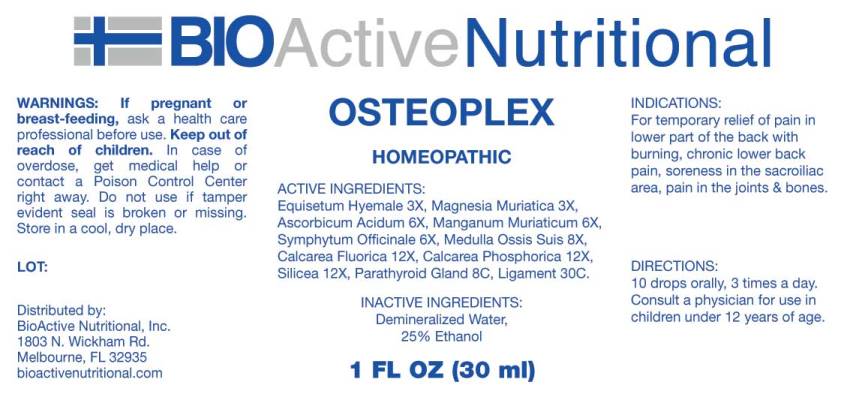 DRUG LABEL: Osteoplex
NDC: 43857-0555 | Form: LIQUID
Manufacturer: BioActive Nutritional, Inc.
Category: homeopathic | Type: HUMAN OTC DRUG LABEL
Date: 20241017

ACTIVE INGREDIENTS: EQUISETUM HYEMALE WHOLE 3 [hp_X]/1 mL; MAGNESIUM CHLORIDE 3 [hp_X]/1 mL; ASCORBIC ACID 6 [hp_X]/1 mL; MANGANESE CHLORIDE 6 [hp_X]/1 mL; COMFREY ROOT 6 [hp_X]/1 mL; SUS SCROFA BONE MARROW 8 [hp_X]/1 mL; CALCIUM FLUORIDE 12 [hp_X]/1 mL; TRIBASIC CALCIUM PHOSPHATE 12 [hp_X]/1 mL; SILICON DIOXIDE 12 [hp_X]/1 mL; SUS SCROFA PARATHYROID GLAND 8 [hp_C]/1 mL; SUS SCROFA LIGAMENT 30 [hp_C]/1 mL
INACTIVE INGREDIENTS: WATER; ALCOHOL

Drug Facts:

ACTIVE INGREDIENTS:

Equisetum Hyemale 3X, Magnesia Muriatica 3X, Ascorbicum Acidum 6X, Manganum Muriaticum 6X, Symphytum Officinale 6X, Medulla Ossis Suis 8X, Calcarea Fluorica 12X, Calcarea Phosphorica 12X, Silicea 12X, Parathyroid Gland (Suis) 8C, Ligament (Suis) 30C.

INDICATIONS:

For temporary relief of pain in lower part of the back with burning, chronic lower back pain, soreness in the sacroiliac area, pain in the joints & bones.

WARNINGS:

If pregnant or breast-feeding, ask a health care professional before use.

Keep out of reach of children. In case of overdose, get medical help or contact a Poison Control Center right away.

Do not use if tamper evident seal is broken or missing.

Store in cool, dry place.

Keep out of reach of children. In case of overdose, get medical help or contact a Poison Control Center right away.

DIRECTIONS:

10 drops orally, 3 times a day. Consult a physician for use in children under 12 years of age.

INDICATIONS:

For temporary relief of pain in lower part of the back with burning, chronic lower back pain, soreness in the sacroiliac area, pain in the joints & bones.

INACTIVE INGREDIENTS:

Demineralized Water, 25% Ethanol

QUESTIONS:

Distributed by:

BioActive Nutritional, Inc.

1803 N. Wickham Rd.

Melbourne, FL 32935

bioactivenutritional.com

PACKAGE LABEL DISPLAY:

BIOActive Nutritional

OSTEOPLEX

HOMEOPATHIC

1 FL OZ (30 ml)